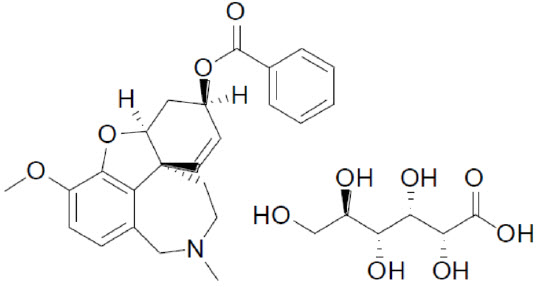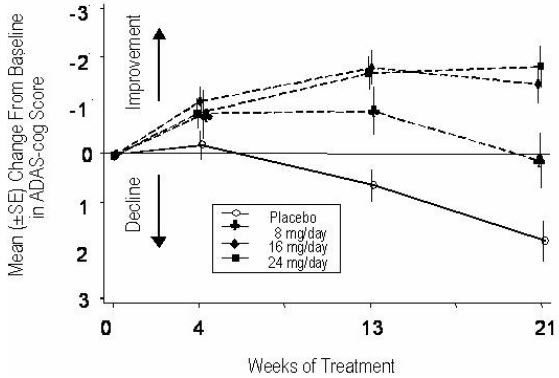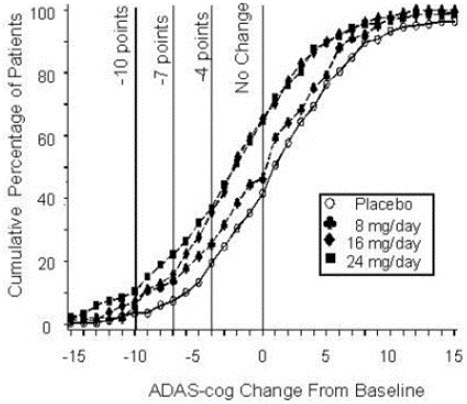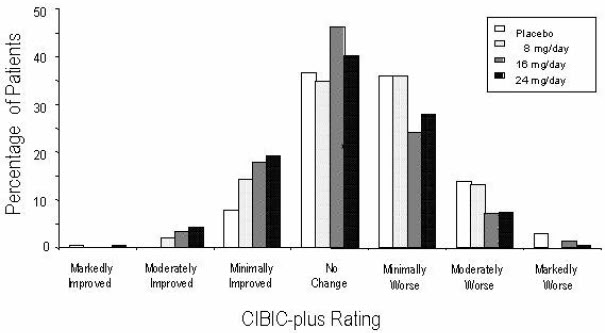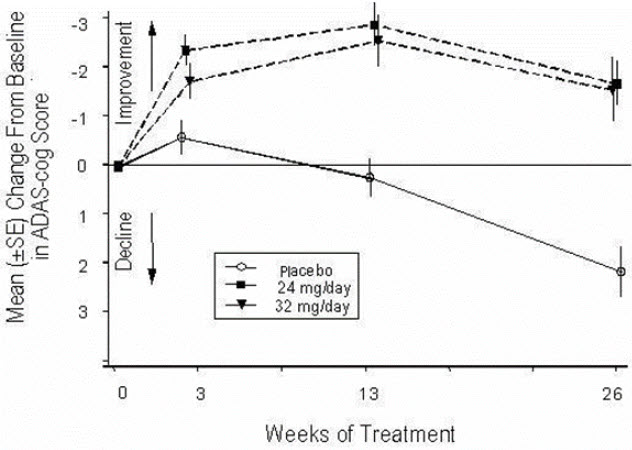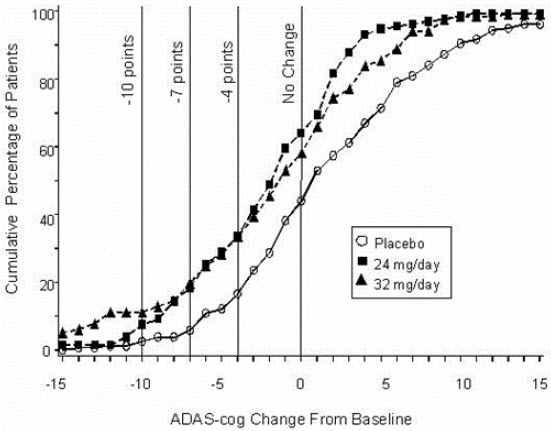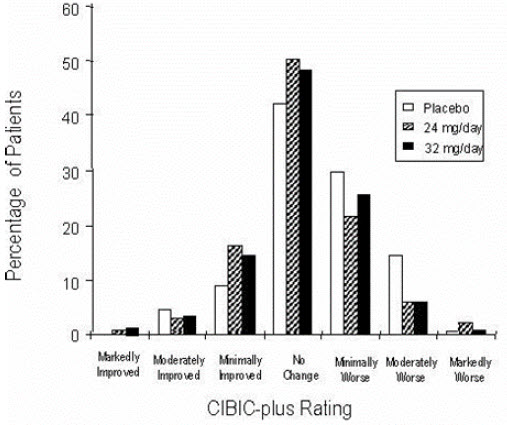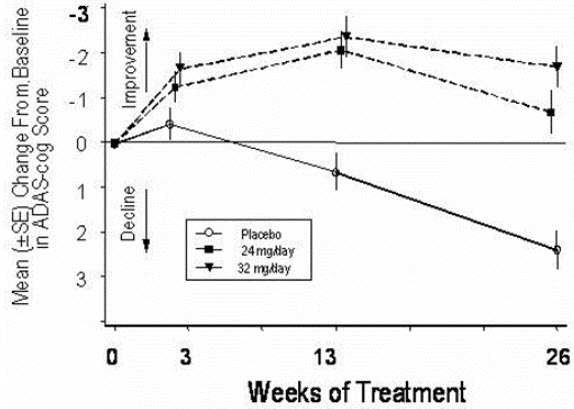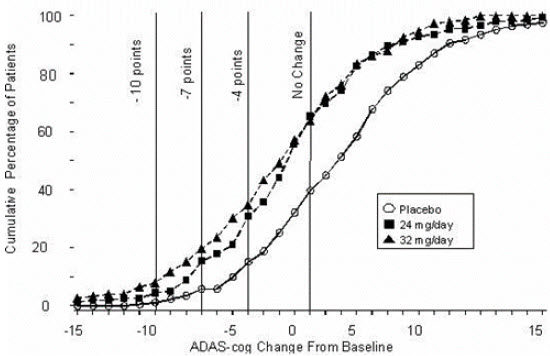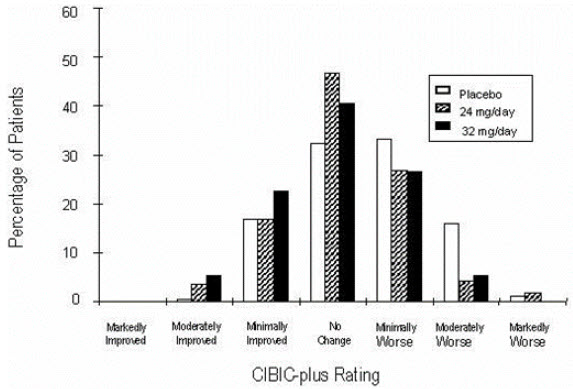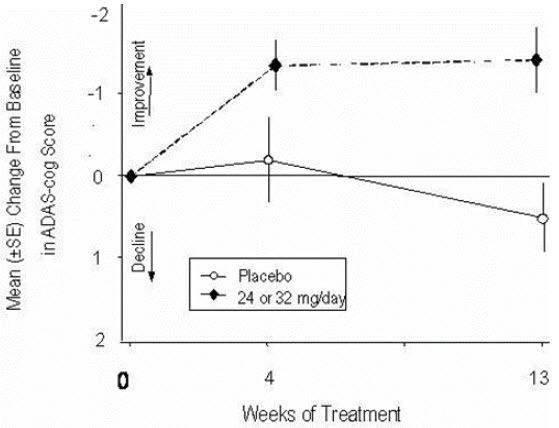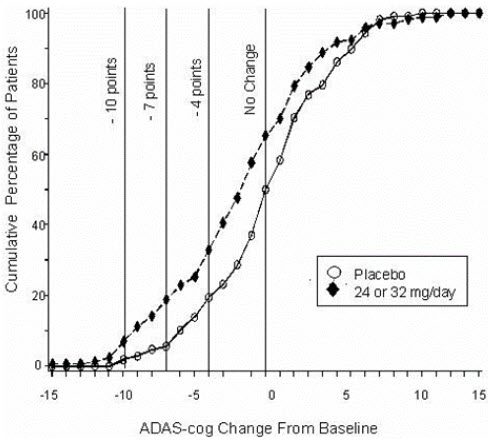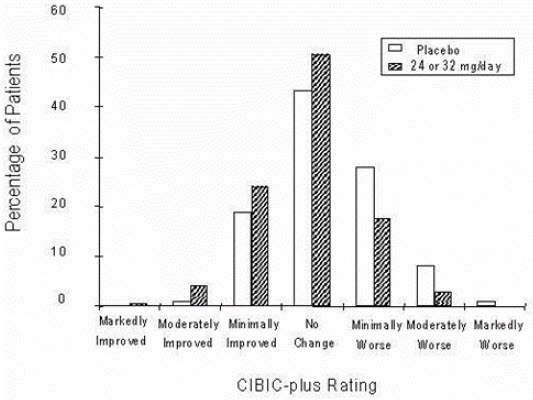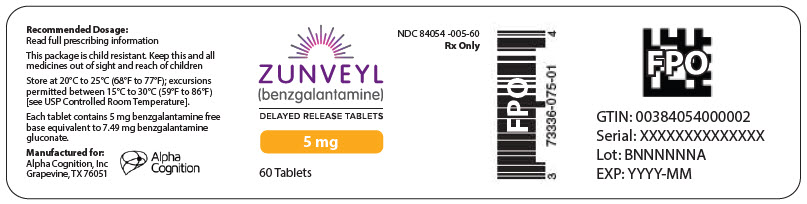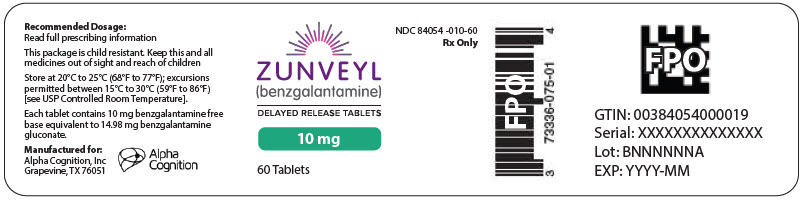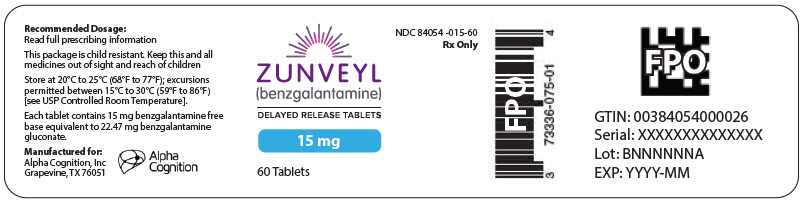 DRUG LABEL: ZUNVEYL
NDC: 84054-005 | Form: TABLET, DELAYED RELEASE
Manufacturer: Alpha Cognition, Inc.
Category: prescription | Type: HUMAN PRESCRIPTION DRUG LABEL
Date: 20250218

ACTIVE INGREDIENTS: benzgalantamine 5 mg/1 1

HIGHLIGHTS OF PRESCRIBING INFORMATION

These highlights do not include all the information needed to use ZUNVEYL safely and effectively. See full prescribing information for ZUNVEYL.
ZUNVEYL (benzgalantamine) delayed-release tablets, for oral use
Initial U.S. Approval: 2001

1 INDICATIONS AND USAGE

ZUNVEYL is a cholinesterase inhibitor indicated for the treatment of mild to moderate dementia of the Alzheimer's type in adults (1)

2 DOSAGE AND ADMINISTRATION

- The recommended starting dosage is 5 mg orally twice daily with or without food; increase to initial maintenance dosage of 10 mg twice daily after a minimum of 4 weeks based on clinical response and tolerability. Dosage may be increased to the maximum recommended dosage of 15 mg twice a day after a minimum of 4 weeks at 10 mg twice daily. (2.1)
- Ensure adequate fluid intake during treatment. Swallow whole; do not split, crush or chew. (2.1)
- May be taken with or without food. (2.1)
- Should not be taken with alcohol. (2.1)
- Hepatic impairment: Should not exceed 10 mg twice daily for moderate hepatic impairment; use in patients with severe hepatic impairment is not recommended (2.2)
- Renal impairment: Should not exceed 10 mg twice daily for creatinine clearance 9 to 59 mL/min; use in patients with creatinine clearance less than 9 mL/min is not recommended. (2.3)

3 DOSAGE FORMS AND STRENGTHS

Delayed-release tablets: 5 mg, 10 mg, and 15 mg (3)

4 CONTRAINDICATIONS

Known hypersensitivity to benzgalantamine, galantamine, or any inactive ingredients in ZUNVEYL (4)

5 WARNINGS AND PRECAUTIONS

- Serious skin reactions: Discontinue at first appearance of skin rash. (5.1)
- All patients should be considered at risk for adverse effects on cardiac conduction, including bradycardia and AV block, because of vagotonic effects on sinoatrial and atrioventricular nodes. (5.3)
- Active or occult gastrointestinal bleeding: Monitor, especially those with an increased risk for developing ulcers. (5.4)
- Cholinomimetics may cause bladder outflow obstruction. (5.5)
- Monitor for respiratory adverse events in patients with a history of severe asthma or obstructive pulmonary disease. (5.7)

6 ADVERSE REACTIONS

The most common adverse reactions with galantamine tablets (≥5%) were nausea, vomiting, diarrhea, dizziness, headache, and decreased appetite. (6.1)

To report SUSPECTED ADVERSE REACTIONS, contact Alpha Cognition Inc. at 1-877-257-4203 or FDA at 1-800-FDA-1088 or www.fda.gov/medwatch.

7 DRUG INTERACTIONS

- Potential to interfere with the activity of anticholinergic medications (7.1)
- Synergistic effect expected when given concurrently with succinylcholine, other cholinesterase inhibitors, similar neuromuscular blocking agents, or cholinergic agonists (7.2)

8 USE IN SPECIFIC POPULATIONS

Pregnancy: Based on animal data may cause fetal harm. (8.1)

FULL PRESCRIBING INFORMATION

1 INDICATIONS AND USAGE

ZUNVEYL is indicated for the treatment of mild to moderate dementia of the Alzheimer's type in adults.

2 DOSAGE AND ADMINISTRATION

2.1 Recommended Dosage and Administration

Dosage

The recommended starting dosage is 5 mg twice a day (10 mg/day) by mouth. Increase to initial maintenance dosage of 10 mg twice daily (20 mg/day) after a minimum of 4 weeks, based on clinical response and tolerability. Dosage may be increased to the maximum recommended dosage of 15 mg twice a day (30 mg/day) after a minimum of 4 weeks at 10 mg twice daily.

Administration

ZUNVEYL can be taken with or without food.

ZUNVEYL should not be taken with alcohol [see Clinical Pharmacology (12.3)].

Swallow whole; do not split, crush or chew.

Ensure adequate fluid intake during treatment.

Interruption of Therapy

If therapy has been interrupted for more than three days, the patient should be restarted at the lowest dosage and the dosage escalated to the current dose.

2.2 Recommended Dosage in Patients with Hepatic Impairment

No dosage adjustment is recommended for patients with mild hepatic impairment (Child-Pugh score of 5-6). In patients with moderate hepatic impairment (Child-Pugh score of 7-9), the dosage should generally not exceed 10 mg twice daily (20 mg/day). The use of ZUNVEYL in patients with severe hepatic impairment (Child-Pugh score of 10-15) is not recommended [see Clinical Pharmacology (12.3)].

2.3 Recommended Dosage in Patients with Renal Impairment

In patients with creatinine clearance of 9 to 59 mL/min, the dosage should generally not exceed 10 mg twice daily (20 mg/day). In patients with creatinine clearance less than 9 mL/min, the use of ZUNVEYL is not recommended [see Clinical Pharmacology (12.3)].

3 DOSAGE FORMS AND STRENGTHS

ZUNVEYL delayed-release tablets are enteric coated and available in the following strengths of benzgalantamine:

- 5 mg white, round, and convex, debossed with "B05" in grey
- 10 mg purple, round, and convex, debossed with "B10" in grey
- 15 mg grey, round, and convex, debossed with "B15" in dark grey

4 CONTRAINDICATIONS

ZUNVEYL is contraindicated in patients with known hypersensitivity to benzgalantamine, galantamine, or to any inactive ingredient in ZUNVEYL. Serious skin reactions have occurred [see Warnings and Precautions (5.1) and Adverse Reactions (6.2)].

5 WARNINGS AND PRECAUTIONS

5.1 Serious Skin Reactions

Serious skin reactions (e.g., Stevens-Johnson syndrome and acute generalized exanthematous pustulosis) have been reported in patients receiving galantamine (the active metabolite of (ZUNVEYL) tablets. Inform patients and caregivers that the use of ZUNVEYL tablets should be discontinued at the first appearance of a skin rash, unless the rash is clearly not drug-related. If signs or symptoms suggest a serious skin reaction, use of this drug should not be resumed, and alternative therapy should be considered [see Contraindications (4)].

5.2 Anesthesia

ZUNVEYL, as a cholinesterase inhibitor, is likely to increase the neuromuscular blocking effects of succinylcholine-type and similar neuromuscular blocking agents during anesthesia.

5.3 Cardiovascular Conditions

Because of their pharmacological action, cholinesterase inhibitors, including ZUNVEYL, have vagotonic effects on the sinoatrial and atrioventricular nodes, leading to bradycardia and AV block. Bradycardia and all types of heart block have been reported in patients taking cholinesterase inhibitors, both with and without known underlying cardiac conduction abnormalities. Therefore, all patients should be considered at risk for adverse effects on cardiac conduction.

Patients treated with galantamine up to 24 mg/day using the recommended dosing schedule showed a dose-related increase in risk of syncope (placebo 0.7% [2/286]; 4 mg twice daily 0.4% [3/692]; 8 mg twice daily 1.3% [7/552]; 12 mg twice daily 2.2% [6/273]).

5.4 Gastrointestinal Conditions

Through their primary action, cholinomimetics, including ZUNVEYL, may be expected to increase gastric acid secretion because of increased cholinergic activity. Therefore, patients should be monitored closely for symptoms of active or occult gastrointestinal bleeding, especially those with an increased risk for developing ulcers (e.g., those with a history of ulcer disease or patients using concurrent nonsteroidal anti-inflammatory drugs [NSAIDs]). Clinical studies of galantamine have shown no increase, relative to placebo, in the incidence of either peptic ulcer disease or gastrointestinal bleeding.

Galantamine, as a predictable consequence of its pharmacological properties, has been shown to produce nausea, vomiting, diarrhea, anorexia, and weight loss [see Adverse Reactions (6.1)]. Monitor the patient's weight during therapy with ZUNVEYL.

5.5 Genitourinary Conditions

Although this was not observed in clinical trials with galantamine, cholinomimetics, including ZUNVEYL, may cause bladder outflow obstruction.

5.6 Neurological Conditions

Cholinesterase inhibitors are believed to have some potential to cause generalized convulsions [see Adverse Reactions (6.2)]. Seizure activity may also be a manifestation of Alzheimer's disease. Patients with Alzheimer's disease should be monitored closely for seizures while taking ZUNVEYL.

5.7 Pulmonary Conditions

Because of its cholinomimetic action, ZUNVEYL should be prescribed with care to patients with a history of severe asthma or obstructive pulmonary disease. Respiratory function should be monitored closely for the occurrence of respiratory adverse reactions.

6 ADVERSE REACTIONS

The following serious adverse reactions are discussed in more detail elsewhere in the labeling:

- Serious Skin Reactions [see Warnings and Precautions (5.1)]
- Cardiovascular Conditions [see Warnings and Precautions (5.3)]
- Gastrointestinal Conditions [see Warnings and Precautions (5.4)]
- Genitourinary Conditions [see Warnings and Precautions (5.5)]
- Neurological Conditions [see Warnings and Precautions (5.6)]
- Pulmonary Conditions [see Warnings and Precautions (5.7)]

6.1 Clinical Trials Experience

Because clinical trials are conducted under widely varying conditions, adverse reaction rates observed in the clinical trials of a drug cannot be directly compared to rates in the clinical trials of another drug and may not reflect the rates observed in practice.

The safety of ZUNVEYL has been established in studies of galantamine immediate-release tablets and galantamine extended-release capsules [see Clinical Studies (14)]. Below is a display of the adverse reactions of galantamine in these studies.

Galantamine Extended-Release Capsules and Immediate-Release Tablets

The safety of the extended-release capsule and immediate-release tablet formulations of galantamine was evaluated in 3956 galantamine-treated patients who participated in 8 placebocontrolled clinical studies and 1454 patients in 5 open-label clinical studies with mild to moderate dementia of the Alzheimer's type. In clinical studies, the safety profile of once-daily treatment with extended-release galantamine was similar in frequency and nature to that seen with immediate-release galantamine. The information presented in this section was derived from pooled double-blind studies and from pooled open-label data.

Commonly-Observed Adverse Reactions in Double-Blind, Placebo-Controlled Clinical Trials of Galantamine

The most common adverse reactions in galantamine-treated patients from double-blind clinical trials (≥5%) were nausea, vomiting, diarrhea, dizziness, headache, and decreased appetite.

Table 1 lists the adverse reactions reported in ≥1% of galantamine-treated patients in 8 placebo-controlled, double-blind clinical trials.

Table 1: Adverse Reactions Reported by ≥1% of Galantamine-Treated Patients in 8 Placebo-Controlled, Double-Blind Clinical Trials
System/Organ Class | Galantamine | Placebo
Adverse Reaction | (n=3956) % | (n=2546) %
Metabolism and Nutrition Disorders
Decreased appetite | 7.4 | 2.1
Psychiatric Disorders
Depression | 3.6 | 2.3
Nervous System Disorders
Dizziness | 7.5 | 3.4
Headache | 7.1 | 5.5
Tremor | 1.6 | 0.7
Somnolence | 1.5 | 0.8
Syncope | 1.4 | 0.6
Lethargy | 1.3 | 0.4
Cardiac Disorders
Bradycardia | 1.0 | 0.3
Gastrointestinal Disorders
Nausea | 20.7 | 5.5
Vomiting | 10.5 | 2.3
Diarrhea | 7.4 | 4.9
Abdominal pain | 3.8 | 2.0
Abdominal discomfort | 2.1 | 0.7
Dyspepsia | 1.5 | 1.0
Musculoskeletal and Connective Tissue Disorders
Muscle spasms | 1.2 | 0.5
General Disorders and Administration Site Conditions
Fatigue | 3.5 | 1.8
Asthenia | 2.0 | 1.5
Malaise | 1.1 | 0.5
Investigations
Decreased weight | 4.7 | 1.5
Injury, Poisoning and Procedural Complications
Fall | 3.9 | 3.0
Laceration | 1.1 | 0.5

The majority of these adverse reactions occurred during the dose-escalation period. In those patients who experienced the most frequent adverse reaction, nausea, the median duration of the nausea was 5-7 days.

Other Adverse Reactions Observed in Clinical Trials of Galantamine

The following adverse reactions occurred in <1% of all galantamine-treated patients (N=3956) in the above double-blind, placebo-controlled clinical trial data sets. In addition, the following also includes all adverse reactions reported at any frequency rate in patients (N=1454) who participated in open-label studies.

Metabolism and Nutrition Disorders: Dehydration

Nervous System Disorders: Dysgeusia, Hypersomnia, Paresthesia

Eye Disorders: Blurred vision

Cardiac Disorders: First degree atrioventricular block, Palpitations, Sinus bradycardia, Supraventricular extrasystoles

Vascular Disorders: Flushing, Hypotension

Gastrointestinal Disorders: Retching

Skin and Subcutaneous Tissue Disorders: Hyperhidrosis

Musculoskeletal and Connective Tissue Disorders: Muscular weakness

Discontinuations Due to Adverse Reactions in Clinical Trials of Galantamine

In the 8 placebo-controlled studies of adults, 418 (10.6%) galantamine-treated patients (N=3956) and 56 (2.2%) placebo patients (N=2546) discontinued because of an adverse reaction. Those reactions with an incidence of ≥0.5% in the galantamine-treated patients included nausea (6.2%), vomiting (3.3%), decreased appetite (1.5%), dizziness (1.3%), diarrhea (0.8%), headache (0.7%), and decreased weight (0.7%). The only event that caused discontinuation with an incidence of ≥0.5% in placebo patients was nausea (17, 0.7%).

In the 5 open-label studies, 103 (7.1%) patients (N=1454) discontinued because of an adverse reaction. Those reactions that caused discontinuation with an incidence of ≥0.5% included nausea (3.0%), vomiting (1.6%), decreased appetite (0.9%), headache (0.8%), decreased weight (0.6%), dizziness (0.6%), and diarrhea (0.5%).

6.2 Postmarketing Experience

The following additional adverse reactions have been identified during postapproval use of galantamine. Because these reactions are reported voluntarily from a population of uncertain size, it is not always possible to reliably estimate their frequency or establish a causal relationship to drug exposure:

Immune System Disorders: Hypersensitivity [see Contraindications (4)]

Psychiatric Disorders: Hallucinations

Nervous System Disorders: Seizures, extrapyramidal disorder [see Warnings and Precautions (5.6)]

Ear and Labyrinth Disorders: Tinnitus

Cardiac Disorders: Complete atrioventricular block

Vascular Disorders: Hypertension

Hepatobiliary Disorders: Hepatitis, increased hepatic enzyme

Skin and Subcutaneous Tissue Disorders: Stevens-Johnson syndrome, acute generalized exanthematous pustulosis [see Warnings and Precautions (5.1)], erythema multiforme

7 DRUG INTERACTIONS

7.1 Use with Anticholinergics

Galantamine has the potential to interfere with the activity of anticholinergic medications.

7.2 Use with Cholinomimetics and Other Cholinesterase Inhibitors

A synergistic effect is expected when cholinesterase inhibitors are given concurrently with succinylcholine, other cholinesterase inhibitors, similar neuromuscular blocking agents or cholinergic agonists such as bethanechol.

8 USE IN SPECIFIC POPULATIONS

8.1 Pregnancy

Risk Summary

There are no adequate data on the developmental risk associated with the use of ZUNVEYL or galantamine in pregnant women. In studies conducted in animals, administration of galantamine during pregnancy resulted in developmental toxicity (increased incidence of morphological abnormalities and decreased growth in offspring) at doses similar to or greater than those used clinically (see Data).

In the U.S. general population, the estimated background risk of major birth defects and miscarriage in clinically recognized pregnancies is 2-4% and 15-20%, respectively. The background risk of major birth defects and miscarriage for the indicated population is unknown.

Data

Animal Data

In rats, administration of galantamine (oral doses of 2, 8, or 16 mg/kg/day), from day 14 (females) or day 60 (males) prior to mating and continuing in females through the period of organogenesis, resulted in an increased incidence of fetal skeletal variations at the two highest doses, which were associated with maternal toxicity. The no-effect dose for embryo-fetal developmental toxicity in rats (2 mg/kg/day) is approximately equal to the maximum recommended human dose (MRHD) of 22 mg/day galantamine (equivalent to 30 mg/day benzgalantamine) on a body surface area (mg/m^2) basis. When galantamine (oral doses of 4, 12, 28, or 40 mg/kg/day) was administered to pregnant rabbits throughout the period of organogenesis, small increases in fetal visceral malformations and skeletal variations were observed at the highest dose which was associated with maternal toxicity. The no-effect dose for embryo-fetal developmental toxicity in rabbits (28 mg/kg/day) is approximately 20 times the MRHD of galantamine on a mg/m2 basis. In a study in which pregnant rats were orally dosed with galantamine (2, 8, or 16 mg/kg/day) from the beginning of organogenesis through day 21 post-partum, pup weights were decreased at birth and during the lactation period at the two highest doses. The no-effect dose for pre- and postnatal developmental toxicity in rats (2 mg/kg/day) is approximately equal to the MRHD of galantamine on a mg/m^2 basis.

8.2 Lactation

Risk Summary

There are no data on the presence of benzgalantamine or galantamine in human milk, the effects on the breastfed infant, or the effects on milk production.

The developmental and health benefits of breastfeeding should be considered along with the mother's clinical need for ZUNVEYL and any potential adverse effects on the breastfed infant from ZUNVEYL or from the underlying maternal condition.

8.4 Pediatric Use

The safety and effectiveness in pediatric patients have not been established.

8.5 Geriatric Use

Eight double-blind, placebo-controlled clinical trials and 5 open-label trials in a total of 6519 patients have investigated galantamine in the treatment of mild to moderate dementia of the Alzheimer's type [see Adverse Reactions (6.1) and Clinical Studies (14)]. The mean age of patients enrolled in these clinical studies was 75 years; 78% of these patients were between 65 and 84 years of age, and 10% of patients were 85 years of age or older. Clinical studies of galantamine did not include sufficient numbers of younger adult patients to determine if patients 65 years of age and older respond differently than younger adult patients.

8.6 Hepatic Impairment

In patients with moderate hepatic impairment, a decrease in clearance of galantamine was observed; therefore, a dosage adjustment is recommended [see Dosage and Administration (2.2) and Clinical Pharmacology (12.3)]. The use of ZUNVEYL in patients with severe hepatic impairment is not recommended.

8.7 Renal Impairment

In patients with a creatinine clearance of 9 to 59 mL/min, an increase in exposure of galantamine was observed; therefore, a dosage adjustment is recommended [see Dosage and Administration (232) and Clinical Pharmacology (12.3)]. The use of ZUNVEYL in patients with creatinine clearance less than 9 mL/min is not recommended.

10 OVERDOSAGE

Because strategies for the management of overdose are continually evolving, it is advisable to contact a poison control center to determine the latest recommendations for the management of an overdose of any drug.

As in any case of overdose, general supportive measures should be utilized. Signs and symptoms of significant overdosing of galantamine are predicted to be similar to those of overdosing of other cholinomimetics. These effects generally involve the central nervous system, the parasympathetic nervous system, and the neuromuscular junction. In addition to muscle weakness or fasciculations, some or all of the following signs of cholinergic crisis may develop: severe nausea, vomiting, gastrointestinal cramping, salivation, lacrimation, urination, defecation, sweating, bradycardia, hypotension, respiratory depression, collapse and convulsions. Increasing muscle weakness is a possibility and may result in death if respiratory muscles are involved.

Tertiary anticholinergics such as atropine may be used as an antidote for ZUNVEYL overdosage. Intravenous (IV) atropine sulfate titrated to effect is recommended at an initial dose of 0.5 to 1.0 mg IV with subsequent doses based upon clinical response. Atypical responses in blood pressure and heart rate have been reported with other cholinomimetics when co-administered with quaternary anticholinergics. It is not known whether galantamine and/or its metabolites can be removed by dialysis (hemodialysis, peritoneal dialysis, or hemofiltration). Dose-related signs of toxicity in animals included hypoactivity, tremors, clonic convulsions, salivation, lacrimation, chromodacryorrhea, mucoid feces, and dyspnea.

In one postmarketing report, one patient who had been taking 4 mg of galantamine daily for a week inadvertently ingested eight 4 mg tablets (32 mg total) on a single day. Subsequently, she developed bradycardia, QT prolongation, ventricular tachycardia and torsades de pointes accompanied by a brief loss of consciousness for which she required hospital treatment. Two additional cases of accidental ingestion of 32 mg (nausea, vomiting, and dry mouth; nausea, vomiting, and substernal chest pain) and one of 40 mg (vomiting), resulted in brief hospitalizations for observation with full recovery. One patient, who was prescribed 24 mg/day and had a history of hallucinations over the previous two years, mistakenly received 24 mg twice daily for 34 days and developed hallucinations requiring hospitalization. Another patient, who was prescribed 16 mg/day of oral solution, inadvertently ingested 160 mg (40 mL) and experienced sweating, vomiting, bradycardia, and near-syncope one hour later, which necessitated hospital treatment. His symptoms resolved within 24 hours.

11 DESCRIPTION

ZUNVEYL (benzgalantamine) is a prodrug of galantamine, an acetylcholinesterase inhibitor . Benzgalantamine gluconate is known chemically as (4aS,6R,8aS)-4a,5,9,10,11,12-hexahydro-3-methoxy-11-methyl-6H-benzofuro[3a,3,2-ef][2]benzazepin-6- benzoate gluconate salt. It has an empirical formula of C30H37NO11 and has a molecular weight of 587.61 (gluconate salt) and 391.46 (benzgalantamine). Benzgalantamine gluconate is a white to pale yellow powder and is soluble in water. Benzgalantamine has a pH of 5 to 6 and dissociation constant (pKa) of 7.0. It is slightly soluble in methanol and practically insoluble in acetone, acetonitrile and hexane. The structural formula for benzgalantamine gluconate is:

ZUNVEYL contains 5 mg, 10 mg, 15 mg benzgalantamine equivalent to 7.49 mg, 14.98 mg, and 22.47 mg benzgalantamine gluconate, respectively. ZUNVEYL delayed-release tablets are for oral use. Inactive ingredients include calcium silicate, colloidal silicon dioxide, hypromellose, magnesium stearate, mannitol, methacrylic acid, poloxamer 407, polyethylene glycol/macrogol, sodium bicarbonate, sodium lauryl sulfate, sodium stearyl fumarate, talc, and titanium dioxide. The 10 mg tablet also contains Carmine, FD&C Blue #2/Indigo Carmine Aluminum Lake, and FD&C Red #40/Allura Red AC Aluminum Lake. The 15 mg tablet also contains FD&C Blue #2/Indigo Carmine Aluminum Lake, FD&C Red #40/Allura Red AC Aluminum Lake, and FD&C Yellow #6/Sunset Yellow FCF Aluminum Lake.

12 CLINICAL PHARMACOLOGY

12.1 Mechanism of Action

Although the etiology of cognitive impairment in Alzheimer's disease (AD) is not fully understood, it has been reported that acetylcholine-producing neurons degenerate in the brains of patients with Alzheimer's disease. The degree of this cholinergic loss has been correlated with degree of cognitive impairment and density of amyloid plaques (a neuropathological hallmark of Alzheimer's disease).

ZUNVEYL is a prodrug of galantamine. Galantamine, a tertiary alkaloid, is a competitive and reversible inhibitor of acetylcholinesterase. While the precise mechanism of galantamine's action is unknown, it is postulated to exert its therapeutic effect by enhancing cholinergic function. This is accomplished by increasing the concentration of acetylcholine through reversible inhibition of its hydrolysis by cholinesterase. If this mechanism is correct, galantamine's effect may lessen as the disease process advances and fewer cholinergic neurons remain functionally intact. There is no evidence that galantamine alters the course of the underlying dementing process.

12.2 Pharmacodynamics

There are no relevant pharmacodynamic (PD) data, and the PD effects are unknown for ZUNVEYL.

12.3 Pharmacokinetics

Benzgalantamine is a prodrug of galantamine, the active metabolite. The systemic exposures of benzgalantamine are less than 1% of galantamine exposures; therefore, the pharmacokinetic information presented below is for that of galantamine. Dose-proportionality is observed for ZUNVEYL over the dose range of 5 to 15 mg and steady state is achieved within a week.

Absorption

Galantamine is absorbed with time to peak concentration of about 2.5 to 3 hours. The absolute bioavailability of galantamine is about 90%.

Effect of Food

Food did not affect the Cmax or AUC of galantamine, but Tmax was 6 hours, when ZUNVEYL was administered with food.

Distribution

The mean volume of distribution of galantamine is 175 L. The plasma protein binding of galantamine is 18% at therapeutically relevant concentrations. In whole blood, galantamine is mainly distributed to blood cells (52.7%). The blood to plasma concentration ratio of galantamine is 1.2.

Elimination

Galantamine is eliminated by hepatic cytochrome P450 enzymes, glucuronidation, and excretion of unchanged drug in the urine.

After IV or oral administration, about 20% of the dose was excreted as unchanged galantamine in the urine in 24 hours, representing a renal clearance of about 65 mL/min, about 20-25% of the total plasma clearance of about 300 mL/min. Galantamine has a terminal half-life of about 7 hours.

Metabolism

Based on in vitro studies, CYP2D6 and CYP3A4 were the major enzymes involved in the metabolism of galantamine. CYP2D6 was involved in the formation of O-desmethylgalantamine, whereas CYP3A4 mediated the formation of galantamine-N-oxide. Galantamine is also glucuronidated and excreted unchanged in urine.

Excretion

In studies of oral 3H-galantamine, unchanged galantamine and its glucuronide, accounted for most plasma radioactivity in poor and extensive CYP2D6 metabolizers. Up to 8 hours post-dose, unchanged galantamine accounted for 39-77% of the total radioactivity in the plasma, and galantamine glucuronide for 14-24%. By 7 days, 93-99% of the radioactivity had been recovered, with about 95% in urine and about 5% in the feces. Total urinary recovery of unchanged galantamine accounted for, on average, 32% of the dose and that of galantamine glucuronide for another 12% on average.

Specific Populations

Elderly

Data from clinical trials in patients with Alzheimer's disease indicate that galantamine concentrations are 30-40% higher in those patients than in healthy young subjects.

Gender and Race

A population pharmacokinetic analysis (on 539 men and 550 women) indicates that galantamine clearance is about 20% lower in women than in men (which is explained by a lower body weight in women) and that race (n=1029 White, 24 Black, 13 Asian, and 23 other) did not affect the clearance of galantamine.

Hepatic Impairment

Following a single 4 mg dose of galantamine tablets, the pharmacokinetics of galantamine in subjects with mild hepatic impairment (n=8; Child-Pugh score of 5-6) were similar to the pharmacokinetics of galantamine in healthy subjects. In patients with moderate hepatic impairment (n=8; Child Pugh score of 7-9), galantamine clearance was decreased by about 25% compared to galantamine clearance in normal volunteers. Exposure to galantamine would be expected to increase further with increasing degree of hepatic impairment [see Dosage and Administration (2.2) and Use in Specific Populations (8.6)].

Renal Impairment

Following a single 8 mg dose of galantamine tablets, AUC increased by 37% and 67% in patients with moderate and severe renal impairment, respectively, compared with normal volunteers [see Dosage and Administration (2.3) and Use in Specific Populations (8.7)].

CYP2D6 Pharmacogenetics

No clinically significant differences in the pharmacokinetics of galantamine were observed based on CYP2D6 metabolizer status.

Drug-Drug Interactions

In Vitro Studies

Effect of Alcohol: Alcohol-induced dose dumping of ZUNVEYL was observed in the presence of 40% (v/v) alcohol in an in vitro dissolution study; however, dose dumping was not observed in the presence of lower alcohol concentrations. The clinical significance of this dose dumping was not fully characterized in humans [see Dosage and Administration (2.1)].

Effect of Other Drugs on Galantamine

- CYP3A4 Inhibitors:
  Ketoconazole
  Ketoconazole, a strong inhibitor of CYP3A4 and an inhibitor of CYP2D6, when administered at a dose of 200 mg two times a day for 4 days, increased the AUC of galantamine by 30%.
  Erythromycin
  Erythromycin, a moderate inhibitor of CYP3A4, when administered at a dose of 500 mg four times a day for 4 days, increased the AUC of galantamine by 10%.

- CYP2D6 Inhibitors:
  A population pharmacokinetics analysis on a database of 852 patients with Alzheimer's disease showed that the clearance of galantamine was reduced about 25-33% by the concurrent administration of amitriptyline (n=17), fluoxetine (n=48), fluvoxamine (n=14), and quinidine (n=7), all of which are known inhibitors of CYP2D6.
  Paroxetine
  Paroxetine, a strong inhibitor of CYP2D6, when administered at a dose of 20 mg/day for 16 days, increased the oral bioavailability of galantamine by about 40%.

- H2 Antagonists
  Galantamine was administered as a single dose of 4 mg on day 2 of a 3-day treatment with either cimetidine (800 mg daily) or ranitidine (300 mg daily). Cimetidine increased the bioavailability of galantamine by approximately 16%. Ranitidine had no effect on the pharmacokinetics of galantamine.

- Memantine
  Memantine, an N-methyl-D-aspartate receptor antagonist, when administered at a dose of 10 mg two times a day, had no effect on the pharmacokinetics of galantamine (16 mg/day) at steady state.

Effect of Galantamine on Other Drugs

- In Vitro Studies
  In vitro studies show that galantamine did not inhibit the metabolic pathways catalyzed by CYP1A2, CYP2A6, CYP3A4, CYP4A, CYP2C, CYP2D6 or CYP2E1.

- In Vivo Studies
  Warfarin
  Multiple doses of galantamine at 24 mg/day had no effect on the pharmacokinetics of R-and S-warfarin (administered in a single dose of 25 mg) or on the increased prothrombin time induced by warfarin. The protein binding of warfarin was unaffected by galantamine.
  Digoxin
  Multiple doses of galantamine at 24 mg/day had no effect on the steady-state pharmacokinetics of digoxin (at a dose of 0.375 mg once daily) when those two drugs were co-administered. In that study, however, one healthy subject was hospitalized on account of 2nd and 3rd degree heart block and bradycardia.

13 NONCLINICAL TOXICOLOGY

13.1 Carcinogenesis, Mutagenesis, Impairment of Fertility

Carcinogenesis

In a 24-month oral carcinogenicity study in rats, an increase in endometrial adenocarcinomas was observed at 10 mg/kg/day (4 times the MRHD of 22 mg/day galantamine (equivalent to 30 mg/day benzgalantamine) on a mg/m2 basis) and 30 mg/kg/day (12 times MRHD of galantamine on a mg/m2 basis). No increase in neoplastic changes was observed in females at 2.5 mg/kg/day (equivalent to the MRHD of galantamine on a mg/m2 basis) or in males up to the highest dose tested of 30 mg/kg/day (12 times the MRHD of galantamine on a mg/m^2 basis).

Galantamine was not carcinogenic in a 6-month carcinogenicity study in transgenic (P 53-deficient) mice at oral doses up to 20 mg/kg/day, or in a 24-month carcinogenicity study in mice at oral doses up to 10 mg/kg/day.

Mutagenesis

Benzgalantamine was negative in a battery of in vitro (bacterial reverse mutation and chromosomal aberration in human peripheral blood lymphocytes) genotoxicity assays.

Galantamine was negative in a battery of in vitro (bacterial reverse mutation, mouse lymphoma tk, and chromosomal aberration in mammalian cells) and in vivo (mouse micronucleus) genotoxicity assays.

Impairment of Fertility

No impairment of fertility was seen in rats given galantamine at up to 16 mg/kg/day (7 times the MRHD of galantamine on a mg/m2 basis) for 14 days prior to mating in females and for 60 days prior to mating in males.

14 CLINICAL STUDIES

The efficacy of ZUNVEYL is based upon 3 bioavailability studies in healthy adults comparing galantamine immediate-release tablets and galantamine extended-release capsules to ZUNVEYL [see Clinical Pharmacology (12.3)].

The effectiveness of galantamine as a treatment for Alzheimer's disease is demonstrated by the results of 5 randomized, double-blind, placebo-controlled clinical investigations in patients with probable Alzheimer's disease, 4 with the immediate-release tablet and 1 with the extendedrelease capsule [diagnosed by NINCDS-ADRDA criteria, with Mini-Mental State Examination scores that were ≥10 and ≤24]. Doses studied with the immediate-release tablet were 8-32 mg/day given as twice daily doses. In 3 of the 4 studies with the immediate-release tablet, patients were started on a low dose of 8 mg, then titrated weekly by 8 mg/day to 24 or 32 mg as assigned. In the fourth study (USA 4-week Dose Escalation Fixed-Dose Study) dose escalation of 8 mg/day occurred over 4-week intervals. The mean age of patients participating in these 4 galantamine trials was 75 years with a range of 41 to 100. Approximately 62% of patients were women and 38% were men. The racial distribution was White 94%, Black 3% and other races 3%. Two other studies examined a three times daily dosing regimen; these also showed or suggested benefit but did not suggest an advantage over twice daily dosing.

14.1 Study Outcome Measures

In each study, the primary effectiveness of galantamine was evaluated using a dual outcome assessment strategy as measured by the Alzheimer's Disease Assessment Scale (ADAS-cog) and the Clinician's Interview Based Impression of Change that required the use of caregiver information (CIBIC-plus).

The ability of galantamine to improve cognitive performance was assessed with the cognitive sub-scale of the Alzheimer's Disease Assessment Scale (ADAS-cog), a multi-item instrument that has been validated in longitudinal cohorts of Alzheimer's disease patients. The ADAS-cog examines selected aspects of cognitive performance including elements of memory, orientation, attention, reasoning, language and praxis. The ADAS-cog scoring range is from 0 to 70, with higher scores indicating greater cognitive impairment. Elderly normal adults may score as low as 0 or 1, but it is not unusual for non-demented adults to score slightly higher.

The patients recruited as participants in each study using the immediate-release tablet formulation had mean scores on ADAS-cog of approximately 27 units, with a range from 5 to 69. Experience using the ADAS-cog in longitudinal studies of ambulatory patients with mild to moderate Alzheimer's disease suggests that patients typically gain 6 to 12 units a year. Because the ADAS-cog is not uniformly sensitive to change over the course of the disease, a less than typical degree of change may be seen in patients at very early or later stages of disease. The annualized rate of decline in the placebo patients participating in galantamine trials was approximately 4.5 units per year.

The ability of galantamine to produce an overall clinical effect was assessed using a Clinician's Interview Based Impression of Change that required the use of caregiver information, the CIBICplus. The CIBIC-plus is not a single instrument and is not a standardized instrument like the ADAS-cog. Clinical trials for investigational drugs have used a variety of CIBIC formats, each different in terms of depth and structure. As such, results from a CIBIC-plus reflect clinical experience from the trial or trials in which it was used and cannot be compared directly with the results of CIBIC-plus evaluations from other clinical trials. The CIBIC-plus used in the trials was a semi-structured instrument based on a comprehensive evaluation at baseline and subsequent time-points of 4 major areas of patient function: general, cognitive, behavioral and activities of daily living. It represents the assessment of a skilled clinician based on his/her observation at an interview with the patient, in combination with information supplied by a caregiver familiar with the behavior of the patient over the interval rated. The CIBIC-plus is scored as a seven-point categorical rating, ranging from a score of 1, indicating "markedly improved," to a score of 4, indicating "no change" to a score of 7, indicating "marked worsening." The CIBIC-plus has not been systematically compared directly to assessments not using information from caregivers (CIBIC) or other global methods.

14.2 Galantamine Immediate-Release Tablets

U.S. Twenty-One Week Fixed-Dose Study

In a study of 21 weeks duration, 978 patients were randomized to doses of 8, 16, or 24 mg of galantamine per day, or to placebo, each given in 2 divided doses. Treatment was initiated at 8 mg/day for all patients randomized to galantamine and increased by 8 mg/day every 4 weeks. Therefore, the maximum titration phase was 8 weeks and the minimum maintenance phase was 13 weeks (in patients randomized to 24 mg/day of galantamine).

Effects on the ADAS-cog

Figure 1 illustrates the time course for the change from baseline in ADAS-cog scores for all four dose groups over the 21 weeks of the study. At 21 weeks of treatment, the mean differences in the ADAS-cog change scores for the galantamine-treated patients compared to the patients on placebo were 1.7, 3.3, and 3.6 units for the 8, 16 and 24 mg/day treatments, respectively. The 16 mg/day and 24 mg/day treatments were statistically significantly superior to placebo and to the 8 mg/day treatment. There was no statistically significant difference between the 16 mg/day and 24 mg/day dose groups.

Figure 1: Time-Course of the Change From Baseline in ADAS-cog Score for Patients Completing 21 Weeks (5 Months) of Treatment

Figure 2 illustrates the cumulative percentages of patients from each of the four treatment groups who had attained at least the measure of improvement in ADAS-cog score shown on the X-axis. Three change scores (10-point, 7-point and 4-point reductions) and no change in score from baseline have been identified for illustrative purposes, and the percent of patients in each group achieving that result is shown in the inset table.

The curves demonstrate that both patients assigned to galantamine and placebo have a wide range of responses, but that the galantamine groups are more likely to show the greater improvements.

Figure 2: Cumulative Percentage of Patients Completing 21 Weeks of Double-Blind Treatment With Specified Changes From Baseline in ADAS-cog Scores. The Percentages of Randomized Patients Who Completed the Study Were: Placebo 84%, 8 mg/day 77%, 16 mg/day 78% and 24 mg/day 78%.

Change in ADAS-cog
Treatment | -10 | -7 | -4 | -0
Placebo | 3.6% | 7.6% | 19.6 % | 41.8%
8 mg/day | 5.9% | 13.9% | 25.7% | 46.5%
16 mg/day | 7.2% | 15.9% | 35.6% | 65.4%
24 mg/day | 10.4% | 22.3% | 37.0% | 64.9%

Effects on the CIBIC-plus

Figure 3 is a histogram of the percentage distribution of CIBIC-plus scores attained by patients assigned to each of the four treatment groups who completed 21 weeks of treatment. The galantamine-placebo differences for these groups of patients in mean rating were 0.15, 0.41 and 0.44 units for the 8, 16 and 24 mg/day treatments, respectively. The 16 mg/day and 24 mg/day treatments were statistically significantly superior to placebo. The differences vs. the 8 mg/day treatment for the 16 and 24 mg/day treatments were 0.26 and 0.29, respectively. There were no statistically significant differences between the 16 mg/day and 24 mg/day dose groups.

Figure 3: Distribution of CIBIC-plus Ratings at Week 21

U.S. Twenty-Six Week Fixed-Dose Study

In a study of 26 weeks duration, 636 patients were randomized to either a dose of 24 mg or 32 mg of galantamine per day, or to placebo, each given in two divided doses. The 26-week study was divided into a 3-week dose titration phase and a 23-week maintenance phase.

Effects on the ADAS-cog

Figure 4 illustrates the time course for the change from baseline in ADAS-cog scores for all three dose groups over the 26 weeks of the study. At 26 weeks of treatment, the mean differences in the ADAS-cog change scores for the galantamine-treated patients compared to the patients on placebo were 3.9 and 3.8 units for the 24 mg/day and 32 mg/day treatments, respectively. Both treatments were statistically significantly superior to placebo but were not significantly different from each other.

Figure 4: Time-Course of the Change From Baseline in ADAS-cog Score for Patients Completing 26 Weeks of Treatment

Figure 5 illustrates the cumulative percentages of patients from each of the three treatment groups who had attained at least the measure of improvement in ADAS-cog score shown on the X-axis. Three change scores (10-point, 7-point and 4-point reductions) and no change in score from baseline have been identified for illustrative purposes, and the percent of patients in each group achieving that result is shown in the inset table.

The curves demonstrate that both patients assigned to galantamine and placebo have a wide range of responses, but that the galantamine groups are more likely to show the greater improvements. A curve for an effective treatment would be shifted to the left of the curve for placebo, while an ineffective or deleterious treatment would be superimposed upon or shifted to the right of the curve for placebo, respectively.

 | Change in ADAS-cog
Treatment | -10 | -7 | -4 | -0
Placebo | 2.1% | 5.7% | 16.6% | 43.9%
24 mg/day | 7.6% | 18.3% | 33.6% | 64.1%
32 mg/day | 11.1% | 19.7% | 33.3% | 58.1%

Figure 5: Cumulative Percentage of Patients Completing 26 Weeks of Double-Blind Treatment With Specified Changes From Baseline in ADAS-cog Scores. The Percentages of Randomized Patients Who Completed the Study Were: Placebo 81%, 24 mg/day 68%, and 32 mg/day 58%.

Effects on the CIBIC-plus

Figure 6 is a histogram of the percentage distribution of CIBIC-plus scores attained by patients assigned to each of the three treatment groups who completed 26 weeks of treatment. The mean galantamine-placebo differences for these groups of patients in the mean rating were 0.28 and 0.29 units for 24 and 32 mg/day of galantamine, respectively. The mean ratings for both groups were statistically significantly superior to placebo but were not significantly different from each other.

Figure 6: Distribution of CIBIC-plus Ratings at Week 26

International Twenty-Six Week Fixed-Dose Study

In a study of 26 weeks duration identical in design to the USA 26-Week Fixed-Dose Study, 653 patients were randomized to either a dose of 24 mg or 32 mg of galantamine per day, or to placebo, each given in two divided doses. The 26-week study was divided into a 3-week dose titration phase and a 23-week maintenance phase.

Effects on the ADAS-cog

Figure 7 illustrates the time course for the change from baseline in ADAS-cog scores for all three dose groups over the 26 weeks of the study. At 26 weeks of treatment, the mean differences in the ADAS-cog change scores for the galantamine-treated patients compared to the patients on placebo were 3.1 and 4.1 units for the 24 mg/day and 32 mg/day treatments, respectively. Both treatments were statistically significantly superior to placebo but were not significantly different from each other.

Figure 7: Time-Course of the Change From Baseline in ADAS-cog Score for Patients Completing 26 Weeks of Treatment

Figure 8 illustrates the cumulative percentages of patients from each of the three treatment groups who had attained at least the measure of improvement in ADAS-cog score shown on the X-axis. Three change scores (10-point, 7-point and 4-point reductions) and no change in score from baseline have been identified for illustrative purposes, and the percent of patients in each group achieving that result is shown in the inset table.

The curves demonstrate that both patients assigned to galantamine and placebo have a wide range of responses, but that the galantamine groups are more likely to show the greater improvements.

Figure 8: Cumulative Percentage of Patients Completing 26 Weeks of Double-Blind Treatment With Specified Changes From Baseline in ADAS-cog Scores. The Percentages of Randomized Patients Who Completed the Study Were: Placebo 87%, 24 mg/day 80%, and 32 mg/day 75%.

Effects on the CIBIC-plus

Figure 9 is a histogram of the percentage distribution of CIBIC-plus scores attained by patients assigned to each of the three treatment groups who completed 26 weeks of treatment. The mean galantamine-placebo differences for these groups of patients in the mean rating of change from baseline were 0.34 and 0.47 for 24 and 32 mg/day of galantamine respectively. The mean ratings for the galantamine groups were statistically significantly superior to placebo but were not significantly different from each other.

Figure 9: Distribution of CIBIC-plus Rating at Week 26

International Thirteen-Week Flexible-Dose Study

In a study of 13 weeks duration, 386 patients were randomized to either a flexible dose of 24-32 mg/day of galantamine or to placebo, each given in two divided doses. The 13-week study was divided into a 3-week dose titration phase and a 10-week maintenance phase. The patients in the active treatment arm of the study were maintained at either 24 mg/day or 32 mg/day at the discretion of the investigator.

Effects on the ADAS-cog

Figure 10 illustrates the time course for the change from baseline in ADAS-cog scores for both dose groups over the 13 weeks of the study. At 13 weeks of treatment, the mean difference in the ADAS-cog change scores for the treated patients compared to the patients on placebo was 1.9. Galantamine at a dose of 24-32 mg/day was statistically significantly superior to placebo.

Figure 10: Time-Course of the Change From Baseline in ADAS-cog Score for Patients Completing 13 Weeks of Treatment

Figure 11 illustrates the cumulative percentages of patients from each of the two treatment groups who had attained at least the measure of improvement in ADAS-cog score shown on the X-axis. Three change scores (10-point, 7-point and 4-point reductions) and no change in score from baseline have been identified for illustrative purposes, and the percent of patients in each group achieving that result is shown in the inset table.

The curves demonstrate that both patients assigned to galantamine and placebo have a wide range of responses, but that the galantamine group is more likely to show the greater improvement.

Figure 11: Cumulative Percentage of Patients Completing 13 Weeks of Double-Blind Treatment With Specified Changes from Baseline in ADAS-cog Scores. The Percentages of Randomized Patients Who Completed the Study Were: Placebo 90%, 24-32 mg/day 67%.

Change in ADAS-cog
Treatment | -10 | -7 | -4 | -0
Placebo | 1.9% | 5.6% | 19.4% | 50.0%
24 or 32 mg/day | 7.1% | 18.8% | 32.9% | 65.3%

Effects on the CIBIC-plus

Figure 12 is a histogram of the percentage distribution of CIBIC-plus scores attained by patients assigned to each of the two treatment groups who completed 13 weeks of treatment. The mean galantamine-placebo differences for the group of patients in the mean rating of change from baseline were 0.37 units. The mean rating for the 24–32 mg/day group was statistically significantly superior to placebo.

Figure 12: Distribution of CIBIC-plus Ratings at Week 13

Age, Gender and Race

Patient's age, gender, or race did not predict clinical outcome of treatment.

14.3 Galantamine Extended-Release Capsules

The efficacy of galantamine extended-release capsules was studied in a randomized, doubleblind, placebo-controlled trial which was 6 months in duration and had an initial 4-week doseescalation phase. In this trial, patients were assigned to one of 3 treatment groups: glantamine extended-release capsules in a flexible dose of 16 to 24 mg once daily; galantamine immediaterelease tablets in a flexible dose of 8 to 12 mg twice daily; and placebo. The primary efficacy measures in this study were the ADAS-cog and CIBIC-plus. On the protocol-specified primary efficacy analysis at Month 6, a statistically significant improvement favoring galantamine extended-release capsules over placebo was seen for the ADAS-cog, but not for the CIBIC-plus. Galantamine extended-release capsules showed a statistically significant improvement when compared with placebo on the Alzheimer's Disease Cooperative Study-Activities of Daily Living (ADCS-ADL) scale, a measure of function, and a secondary efficacy measure in this study. The effects of both galantamine extended-release capsules and galantamine immediaterelease tablets on the ADAS-cog, CIBIC-plus, and ADCS-ADL were similar in this study.

16 HOW SUPPLIED/STORAGE AND HANDLING

16.1 How Supplied

ZUNVEYL delayed-release tablets are enteric coated and supplied in child-resistant packages as follows:

- 5 mg white tablet debossed with "B05" in grey – bottles of 60 (NDC 84054-005-60)
- 10 mg purple tablet debossed with "B10" in grey – bottles of 60 (NDC 84054-010-60)
- 15 mg grey tablet debossed with "B15" in dark grey – bottles of 60 (NDC 84054-015-60)

16.2 Storage and Handling

Store ZUNVEYL delayed-release tablets at 20°C to 25°C (68°F to 77°F); excursions permitted between 15°C to 30°C (59°F to 86°F) [see USP Controlled Room Temperature].

17 PATIENT COUNSELING INFORMATION

Serious Skin Reactions

Advise patients and caregivers to discontinue ZUNVEYL and seek immediate medical attention at the first appearance of skin rash [see Warnings and Precautions (5.1)].

Administration Information

Instruct patients or caregivers about the recommended dosage and administration of ZUNVEYL delayed-release tablets, which should be administered twice daily with or without food.

Instruct patients to swallow ZUNVEYL whole and not to split, crush, or chew the tablets.

Advise patients and caregivers to ensure adequate fluid intake during treatment and that ZUNVEYL should not be taken with alcohol [see Dosage and Administration (2.1)].

Active ingredient made in Taiwan.

ZUNVEYL delayed-release tablets are manufactured for:

Alpha Cognition, Inc.
1452 Hughes Rd
Suite 200
Grapevine, TX 76051

PRINCIPAL DISPLAY PANEL - 5 mg Tablet Bottle Label

NDC 84054 -005-60
Rx Only

ZUNVEYL
(benzgalantamine)

DELAYED RELEASE TABLETS

5 mg

60 Tablets

PRINCIPAL DISPLAY PANEL - 10 mg Tablet Bottle Label

NDC 84054 -010-60
Rx Only

ZUNVEYL
(benzgalantamine)

DELAYED RELEASE TABLETS

10 mg

60 Tablets

PRINCIPAL DISPLAY PANEL - 15 mg Tablet Bottle Label

NDC 84054 -015-60
Rx Only

ZUNVEYL
(benzgalantamine)

DELAYED RELEASE TABLETS

15 mg

60 Tablets